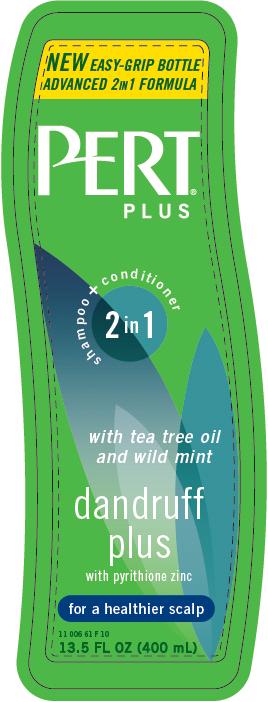 DRUG LABEL: Pert Plus Dandruff Plus
NDC: 41595-5526 | Form: SHAMPOO, SUSPENSION
Manufacturer: Idelle Labs, Ltd
Category: otc | Type: HUMAN OTC DRUG LABEL
Date: 20101229

ACTIVE INGREDIENTS: PYRITHIONE ZINC 0.45 mL/100 mL
INACTIVE INGREDIENTS: WATER; AMMONIUM LAURETH-5 SULFATE; AMMONIUM LAURYL SULFATE; GLYCOL DISTEARATE; DIMETHICONE; CETYL ALCOHOL; COCO MONOETHANOLAMIDE; SODIUM CITRATE; SODIUM BENZOATE; POLYETHYLENE GLYCOL 7000; POLYQUATERNIUM-10 (400 CPS AT 2%); BENZYL ALCOHOL; SODIUM CHLORIDE; CITRIC ACID MONOHYDRATE; METHYLISOTHIAZOLINONE; METHYLCHLOROISOTHIAZOLINONE; FD&C BLUE NO. 1; D&C YELLOW NO. 10; TEA TREE OIL; SAFFLOWER OIL; MINT; OAT; LEVOMENOL

Pert Plus Dandruff Plus

Pert Plus Dandruff Plus 2 in 1 Shampoo and Conditioner
with tea tree oil and wild mint
with pyrithione zinc
for a healthier scalp
MM1

Active Ingredient

Zinc Pyrithione 0.45%

Purpose:

Anti-Dandruff

Uses

Controls the symptoms of dandruff.

Warning:

For external use only

When using this product

avoid contact with eyes. If contact occurs, rinse eyes thoroughly with water.

Stop use and ask a doctor

if condition worsens or does not improve after regular use of this product as directed.

Keep this and all drugs out of reach of children.

If swallowed, get medical help or contact a Poison Control Center right away.

Directions:

For best results, use at least twice a week or as directed by a doctor. Gently massage into wet hair, lather and rinse. Repeat if desired.

Inactive Ingredients:

water, ammonium laureth sulfate, ammonium lauryl sulfate, glycol distearate, dimethicone, glycerin (and) Avena Sativa (oat) kernel extract, bisabolol, fragrance, Melaleuca Alternifolia (tea tree) leaf oil, Carthamus Tinctorius (safflower) seed oil, and Mentha Arvensis (wild mint) leaf extract, cetyl alcohol, cocamide MEA, sodium chloride, guar hydroxypropyltrimonium chloride, hydrogenated polydecene, sodium citrate, sodium benzoate, polyquaternium 10, PEG-7M, trimethylolpropane tricaprylate/tricaprate, citric acid, benzyl alcohol, methylchloroisothiazolinone, methylisothiazolinone, ammonium xylene sulfonate, D&C Yellow No. 10, FD&C Blue No. 1.

Questions?

1-800-487-7273 or visit us at www.pertplus.com

©2011 Idelle Labs, Ltd. All rights reserved
Made in the Canada and distributed by Idelle Labs, Ltd., El Paso, TX 79912

label